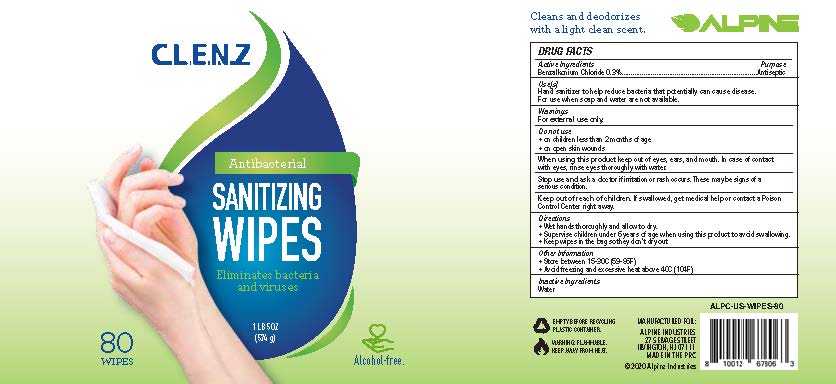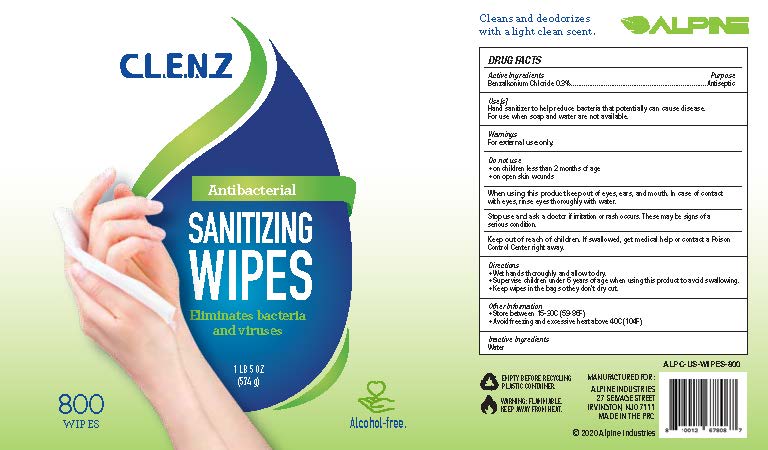 DRUG LABEL: Alpine Clenz Unscented Wipes
NDC: 78224-004 | Form: SWAB
Manufacturer: Alpine Industries
Category: otc | Type: HUMAN OTC DRUG LABEL
Date: 20201202

ACTIVE INGREDIENTS: BENZALKONIUM CHLORIDE 0.3 g/1 1
INACTIVE INGREDIENTS: WATER

Alpine Clenz Unscented Wipes

Active Ingredient

Benzalkonium Chloride 0.3%

Purpose

Antiseptic

Uses

Hand Sanitizer to help reduce bacteria that potentially can cause disease.

For use when soap and water are not available

Warnings

For External use only.

Do not use

on children less than 2 months of age

on open skin wounds

When using this product

keep out of eyes, ears, and mouth, in case of contact with eyes, rinse eyes thoroughly with water

Stop use and ask a doctor.

if irritation or rash occurs. These may be signs of a serious condition.

Keep out of reach of children.

If swallowed, get medical help or contact a Poison Control Center right away

Directions

Wet hands thoroughly and allow to dry
Supervise children under 6 years of age when using this product to avoid swallowing
Keep wipes in the bag so they don't dry out

Other Information

Store between 15-30C (59-86F)
Avoid freezing and excessive heat above 40C (104F)

Inactive Ingredients

Water